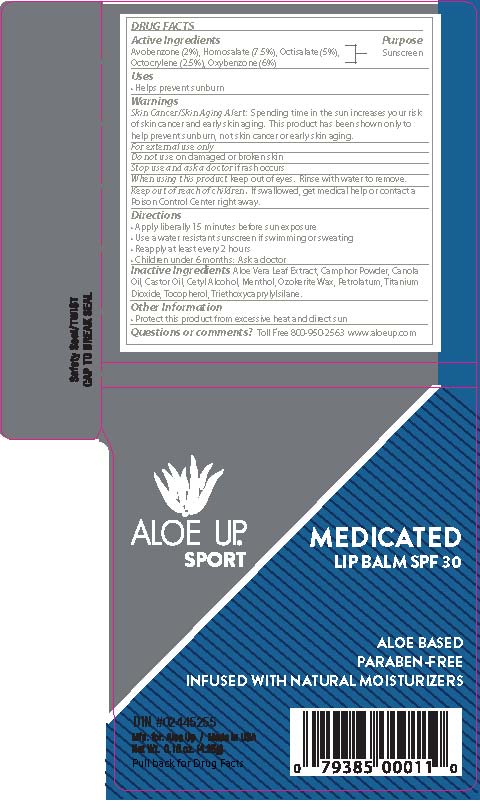 DRUG LABEL: ALOE UP MEDICATED LIP BALM
NDC: 61477-224 | Form: LIPSTICK
Manufacturer: Aloe Care International, LLC
Category: otc | Type: HUMAN OTC DRUG LABEL
Date: 20260130

ACTIVE INGREDIENTS: AVOBENZONE 2 g/100 g; HOMOSALATE 7.5 g/100 g; OCTISALATE 5 g/100 g; OCTOCRYLENE 2.5 g/100 g; OXYBENZONE 6 g/100 g
INACTIVE INGREDIENTS: ALOE VERA LEAF; CAMPHOR (SYNTHETIC); CANOLA OIL; CETYL ALCOHOL; MENTHOL; CERESIN; PETROLATUM; TITANIUM DIOXIDE; TOCOPHEROL; TRIETHOXYCAPRYLYLSILANE

ALOE UP SPORT - MEDICATED LIP BALM SPF-30 (61477-224)

ACTIVE INGREDIENTS

AVOBENZONE (2%)

HOMOSALATE (7.5%)

OCTISALATE (5%)

OCTOCRYLENE (2.5%)

OXYBENZONE (6%)

PURPOSE

SUNSCREEN

USES

HELPS PREVENT SUNBURN.

DIRECTIONS

• Apply liberally 15 minutes before sun exposure
• Use a water resistant sunscreen if swimming or sweating
• Reapply at least every 2 hours
• Children under 6 months: Ask a doctor

Keep out of reach of children. If swallowed, get medical help or contact a Poison Control Center right away.

WARNINGS

Skin Cancer/Skin Aging Alert: Spending time in the sun increases your risk of skin cancer and early skin aging. This product has been shown only to help prevent sunburn, not skin cancer or early skin aging.
For external use only
Do not use on damaged or broken skin
Stop use and ask a doctor if rash occurs
When using this product keep out of eyes. Rinse with water to remove.

INACTIVE INGREDIENTS

Aloe Vera Leaf Extract, Camphor Powder, Canola Oil, Castor Oil, Cetyl Alcohol, Menthol, Ozokerite Wax, Petrolatum, Titanium
Dioxide, Tocopherol, Triethoxycaprylylsilane.

OTHER INFORMATION

• Protect this product from excessive heat and direct sun

QUESTIONS OR COMMENTS?

Toll Free 800-950-2563 www.aloeup.com